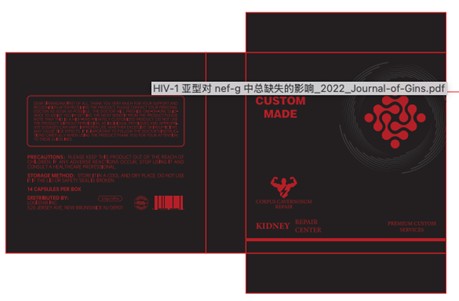 DRUG LABEL: Kidney Repair Center
NDC: 85312-003 | Form: GRANULE
Manufacturer: Panatural Life Science, Inc.
Category: homeopathic | Type: HUMAN OTC DRUG LABEL
Date: 20250310

ACTIVE INGREDIENTS: OCTYLDIMETHYLAMINE OXIDE 60 mg/400 mg; ZINC CITRATE 20 mg/400 mg; ASIAN GINSENG 20 mg/400 mg; PACIFIC OYSTER 30 mg/400 mg; ARGININE 10 mg/400 mg; NIACIN 18 mg/400 mg; SELENOCYSTEINE 20 mg/400 mg; CITRULLINE MALATE 10 mg/400 mg
INACTIVE INGREDIENTS: CALCIUM GLUCONATE; STARCH, CORN; SILICON DIOXIDE; MAGNESIUM STEARATE

Active ingredients (Strength)

Niacin 18mg，L-arginine 10mg，Citrulline malate 10mg，Zinc citrate 20mg，Maca root extract 60mg，Oyster concentrated powder 30mg，Selenium-rich yeast 20mg，Ginseng Extract 20mg

Inactive ingredients

Heavy calcium gluconate 60mg，cornstarch 144mg，silicon dioxide 4mg，Magnesium stearate 4mg

WARINING

Storage instructions: Store it in a cool and dry place. Do not use it if the lid or safety seal is broken.

OTC-PURPOSE

Corpus Cavernosum Repair

iNDICATIONS

Dear Sir/Madam,first of all, thank you very much for your support and recognition.

After receiving the product, please contact your personal doctor as soon as possible. The doctor will provide one-on-one guidance to assist you in getting the most benefit from the product.Please note that this is a high-end privately customized product. Do not use the product without permission, as individual physiques and appropriate dosages can vary. Improper use, whether excessive or insufficient, may cause side effects. It is important to follow the doctor's instructions carefully when using the product.

Thank you for your attention to these guidelines.

keep out of reach of children section

Precautions：Please keep this product out of the reach of children. If any adverse reactions occur, stop using it and consult a healthcare professional.

Dosage

Please note that this is a high-end privately customized product. Do not use the product without permission, as individual physiques and appropriate dosages can vary. Improper use, whether excessive or insufficient, may cause side effects. It is important to follow the doctor's instructions carefully when using the product.

Thank you for your attention to these guidelines.

When

After receiving the product, please contact your personal doctor as soon as possible. The doctor will provide one-on-one guidance to assist you in getting the most benefit from the product.Please note that this is a high-end privately customized product. Do not use the product without permission, as individual physiques and appropriate dosages can vary. Improper use, whether excessive or insufficient, may cause side effects. It is important to follow the doctor's instructions carefully when using the product.

Stop use

Blood in urine, fever, nausea, vomiting, pain in kidney area or acute urinary retention
may be serious.
Consult a doctor promptly if any of these symptoms occur.